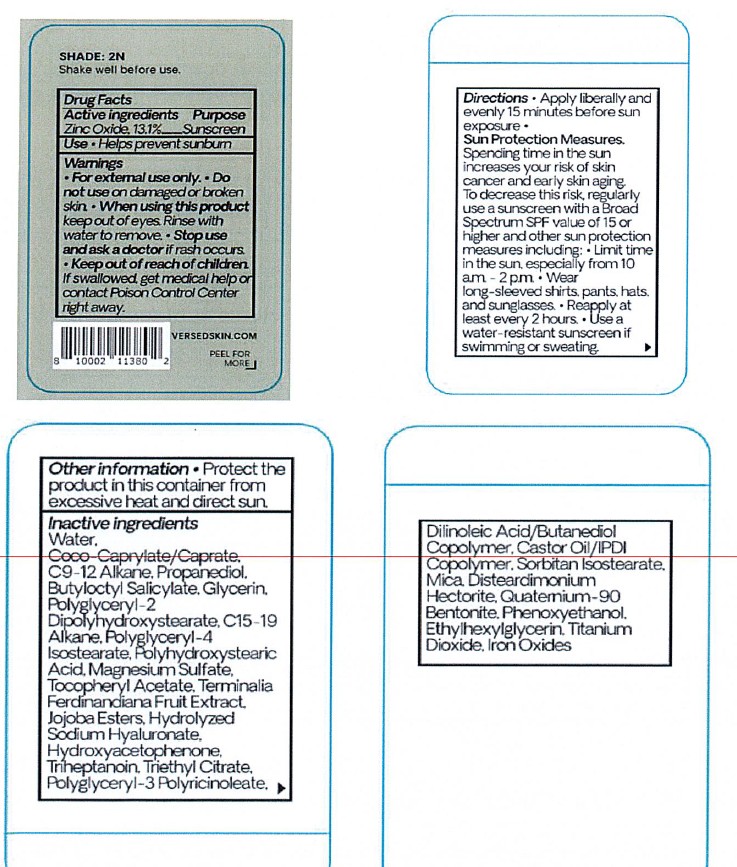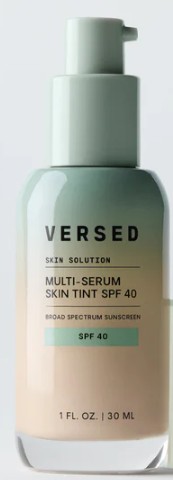 DRUG LABEL: VERSED MULTI SERUM SKIN TINT SPF 40 LIGHT NEUTRAL
NDC: 68577-205 | Form: LOTION
Manufacturer: COSMAX USA, CORP
Category: otc | Type: HUMAN OTC DRUG LABEL
Date: 20251222

ACTIVE INGREDIENTS: ZINC OXIDE 13.1 mg/100 mL
INACTIVE INGREDIENTS: COCO-CAPRYLATE/CAPRATE; C9-12 ALKANE; PROPANEDIOL; POLYHYDROXYSTEARIC ACID (2300 MW); MAGNESIUM SULFATE; ALPHA-TOCOPHEROL ACETATE; DILINOLEIC ACID/BUTANEDIOL COPOLYMER; CASTOR OIL/IPDI COPOLYMER; SORBITAN ISOSTEARATE; TITANIUM DIOXIDE; FERROUS OXIDE; POLYGLYCERYL-3 PENTARICINOLEATE; BUTYLOCTYL SALICYLATE; POLYGLYCERYL-2 DIPOLYHYDROXYSTEARATE; QUATERNIUM-90 BENTONITE; PHENOXYETHANOL; SODIUM HYALURONATE; C15-19 ALKANE; KAKADU PLUM; JOJOBA OIL, RANDOMIZED; POLYGLYCERYL-4 ISOSTEARATE; ETHYLHEXYLGLYCERIN; DISTEARDIMONIUM HECTORITE; TRIETHYL CITRATE; MICA; HYDROXYACETOPHENONE; TRIHEPTANOIN; WATER; GLYCERIN

VERSED MULTI-SERUM SKIN TINT SPF 40_ LIGHT NEUTRAL (2N)

Active ingredients

Zinc Oxide 13.1%

Purpose

Sunscreen

USES

Use

- Helps prevent sunburn

Warnings

- For external use only

Do not useon damaged or broken skin

WHEN USING

When using this productkeep out of eyes. Rinse with water to remove

Stop use and ask a doctorif rash occurs.

Keep out of reach of children.If swallowed, get medical help or contact Poison Control Center right away.

DIRECTIONS

- Apply liberally and evenly 15 minutes before sun exposure
- Sun Protection Measures.Spending time in the sun increases your risk of skin cancer and early skin aging. To decrease this risk, regularly use a sunscreen with a Broad Spectrum SPF valuer of 15 or higher and other sun protection measures including:
- Limit time in the sun, especially from 10 a.m. - 2 p.m.
- Wear long-sleeved shirts, pants, hats, and sunglasses
- Reapply at least every 2 hours
- Use a water-resistant sunscreen if swimming or sweating

OTHER INFORMATION

- Protect the product in this container from excessive heat and direct sun

Inactive ingredients

Water, Coco-Caprylate/Caprate, C9-12 Alkane, Propanediol, Butyloctyl Salicylate, Glycerin, Polyglyceryl-2 Dipolyhydroxystearate, C15-19 Alkane, Polyglyceryl-4 Isostearate, Polyhydroxystearic Acid, Magnesium Sulfate, Tocopheryl Acetate, Terminalia Ferdinandiana Fruit Extract, Jojoba Esters, Hydrolyzed Sodium Hyaluronate, Hydroxyacetophenone, Triheptanoin, Triethyl Citrate, Polyglyceryl-3 Polyricinoleate, Dilinoleic Acid/Butanediol Copolymer, Castor Oil/IPDI Copolymer, Sorbitan Isostearate, Mica, Disteardimonium Hectorite, Quaternium-90 Bentonite, Phenoxyethanol, Ethylhexylglycerin, Titanium Dioxide, Iron Oxides.